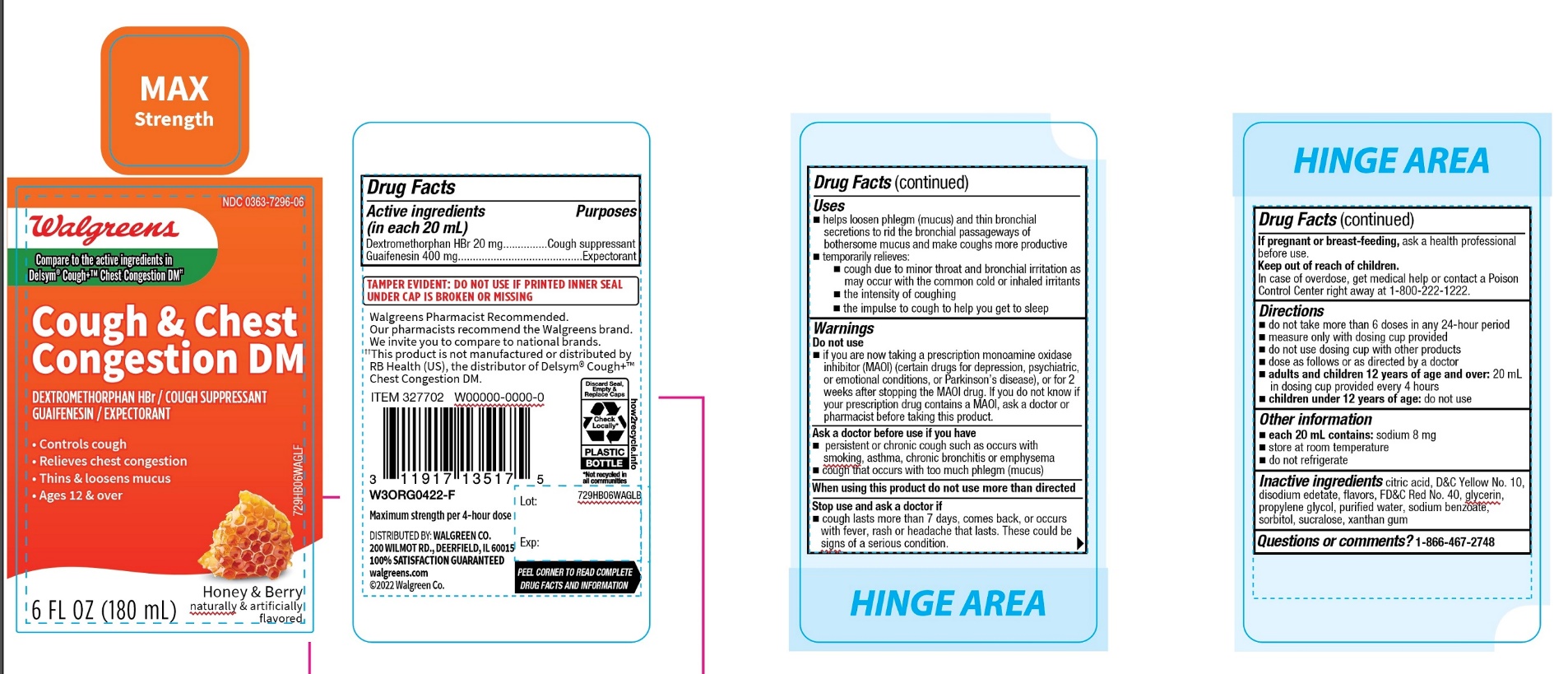 DRUG LABEL: Walgreen

NDC: 0363-7296 | Form: SOLUTION
Manufacturer: WALGREEN COMPANY
Category: otc | Type: HUMAN OTC DRUG LABEL
Date: 20251126

ACTIVE INGREDIENTS: DEXTROMETHORPHAN HYDROBROMIDE 20 mg/20 mL; GUAIFENESIN 400 mg/20 mL
INACTIVE INGREDIENTS: ANHYDROUS CITRIC ACID; D&C YELLOW NO. 10; EDETATE DISODIUM; FD&C RED NO. 40; GLYCERIN; PROPYLENE GLYCOL; WATER; SODIUM BENZOATE; SORBITOL; SUCRALOSE; XANTHAN GUM

Cough & Chest Congestion

Drug Facts

ACTIVE INGREDIENT

PURPOSE

Active ingredients (in each 20 mL) | Purposes
Dextromethorphan HBr 20 mg | Cough suppressant
Guaifenesin 400 mg | Expectorant

Uses

- helps loosen phlegm (mucus) and thin bronchial secretions to rid the bronchial passageways of bothersome mucus and make coughs more productive
- temporarily relieves:
  - cough due to minor throat and bronchial irritation as may occur with the common cold or inhaled irritants
  - the intensity of coughing
  - the impulse to cough to help you get to sleep

Warnings

DO NOT USE

Do not useif you are now taking a prescription monoamine oxidase inhibitor (MAOI) (certain drugs for depression, psychiatric, or emotional conditions, or Parkinson's disease), or for 2 weeks after stopping the MAOI drug. If you do not know if your prescription drug contains an MAOI, ask a doctor or pharmacist before taking this product.

Ask a doctor before use if you have

- persistent or chronic cough such as occurs with smoking, asthma, chronic bronchitis, or emphysema
- cough that occurs with too much phlegm (mucus)

When using this product do not use more than directed

Stop use and ask a doctor if

- cough lasts more than 7 days, comes back, or occurs with fever, rash, or headache that lasts. These could be signs of a serious condition.

PREGNANCY OR BREAST FEEDING

If pregnant or breast-feeding,ask a health professional before use.

Keep out of reach of children.

In case of overdose, get medical help or contact a Poison Control Center right away.

Directions

- do not take more than 6 doses in any 24-hour period
- measure only with dosing cup provided
- do not use dosing cup with other products
- dose as follows or as directed by a doctor
- adults and children 12 years of age and over:20 mL in dosing cup provided every 4 hours
- children under 12 years of age:do not use

Other information

- each 20 mL contains:sodium 8 mg
- store at room temperature
- do not refrigerate

Inactive ingredients

citric acid, D&C Yellow No. 10, disodium edetate, flavors, FD&C Red no. 40, glycerin, propylene glycol, purified water, sodium benzoate, sorbitol, sucralose, xanthan gum

Questions or comments?

1-866-467-2748

PRINCIPAL DISPLAY PANEL - 180 mL Bottle Label

NDC 0363-7296-06

COUGH &
CHEST
CONGESTION

Dextromethorphan HBr (Cough Suppressant)
Guaifenesin (Expectorant)

- Controls Cough
- Relieves Chest Congestion
- Thins & Loosens Mucus

Honey & Berry Flavor

Naturally and Artificially Flavored

6 fl oz (180 mL)

For Ages 12+

Tamper evident: Do not use if printed inner seal under cap is broken or missing.

Maximum Strength per 4-hour dose

Distributed by: